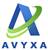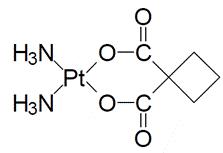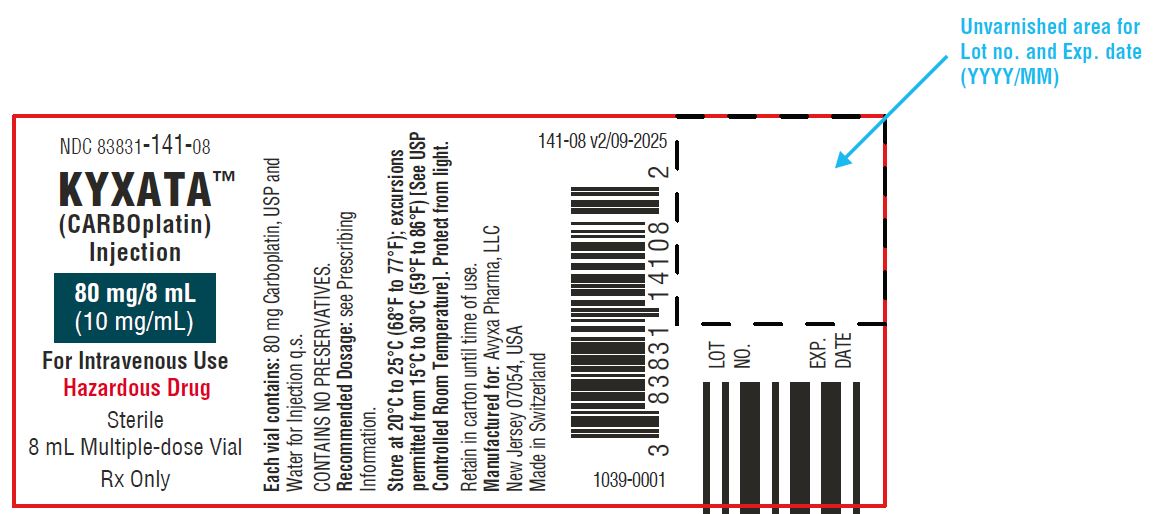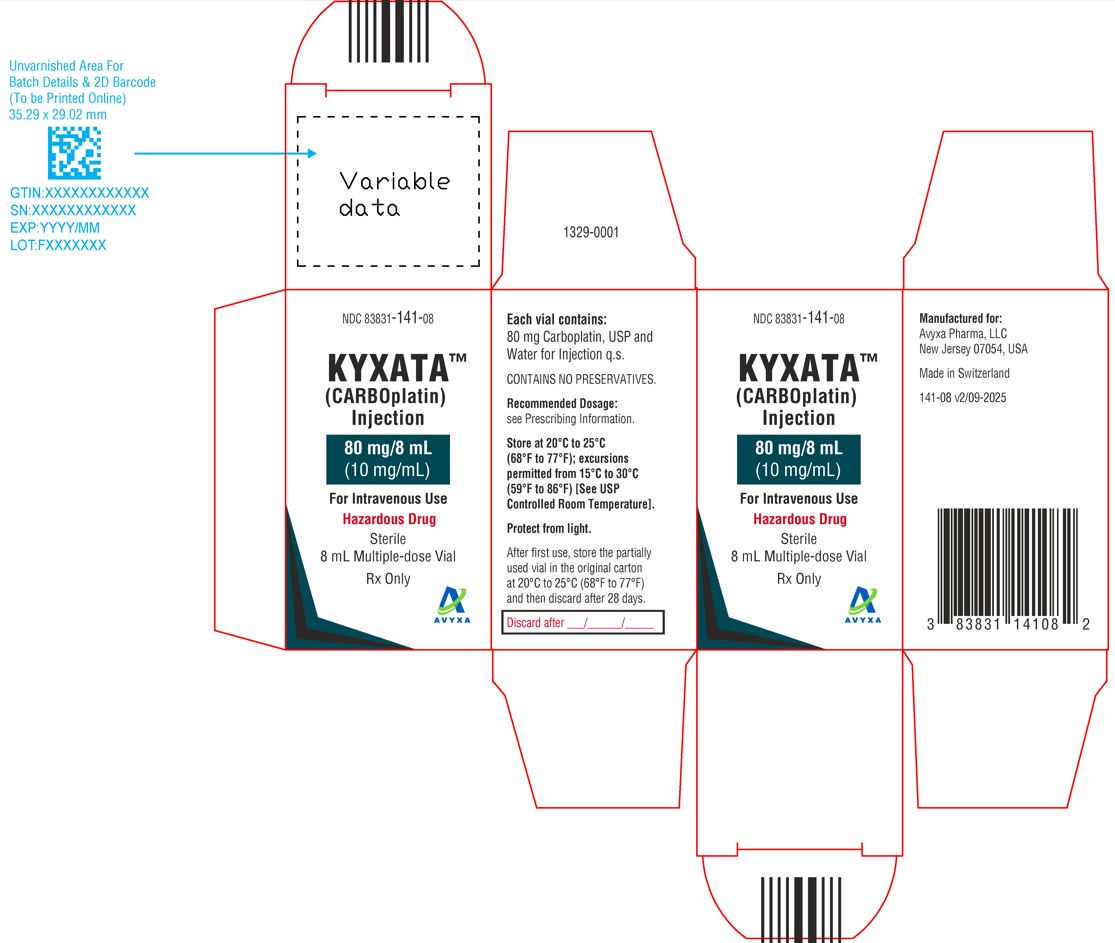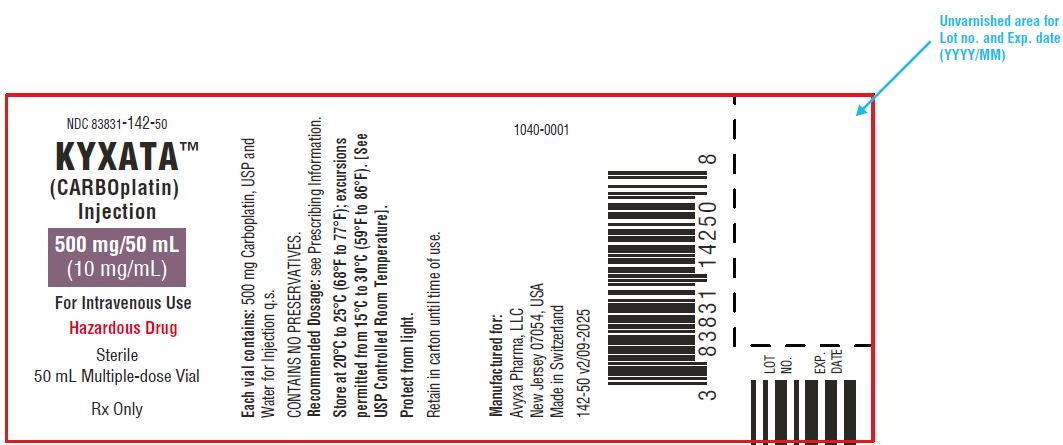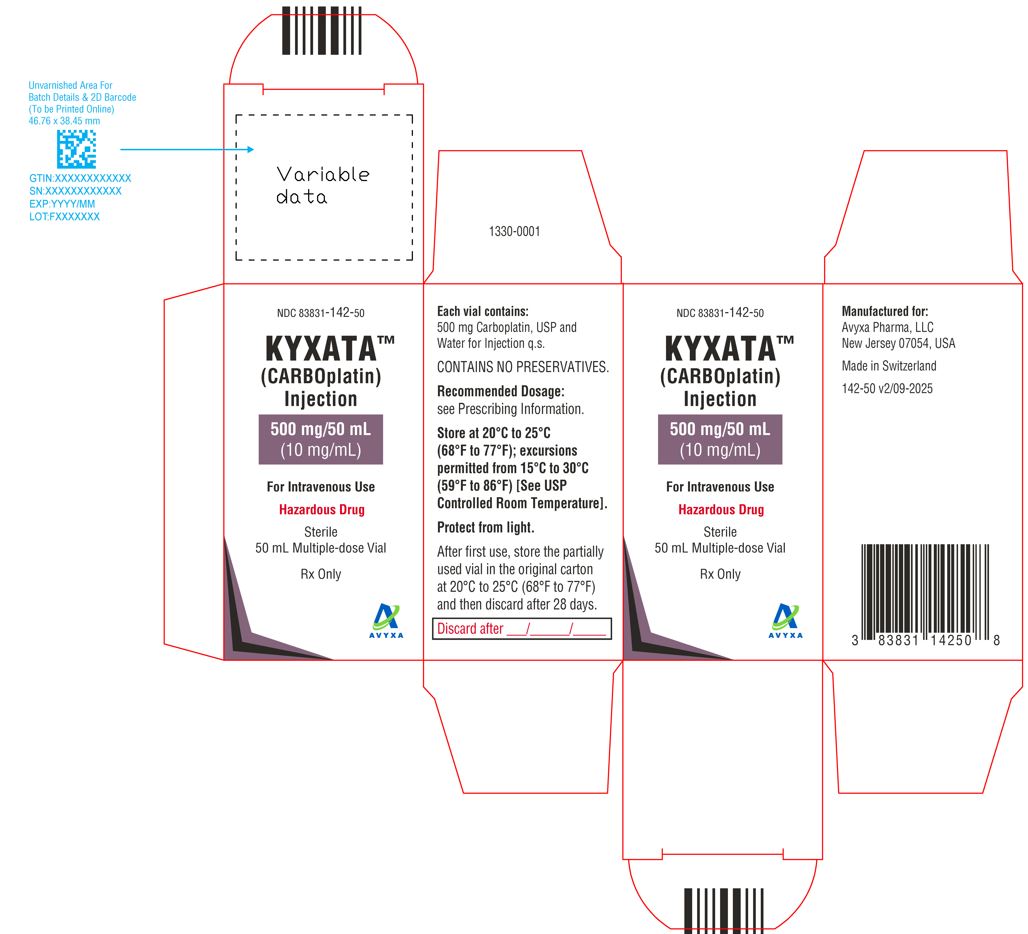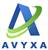 DRUG LABEL: KYXATA
NDC: 83831-140 | Form: INJECTION
Manufacturer: Avyxa Pharma, LLC
Category: prescription | Type: HUMAN PRESCRIPTION DRUG LABEL
Date: 20250902

ACTIVE INGREDIENTS: CARBOPLATIN 20 mg/2 mL
INACTIVE INGREDIENTS: WATER

HIGHLIGHTS OF PRESCRIBING INFORMATION

These highlights do not include all the information needed to use KYXATA safely and effectively. See full prescribing information for KYXATA.
KYXATATM (carboplatin) injection, for intravenous use
Initial U.S. Approval: 2003

WARNING: HYPERSENSITIVITY REACTIONS, INCLUDING ANAPHYLAXIS

- Serious and life-threatening hypersensitivity reactions, including anaphylaxis, can occur with KYXATA within minutes of administration during any cycle. (5.1)
- Immediately withhold KYXATA for severe hypersensitivity reactions and administer appropriate treatment for management of the hypersensitivity reaction. (5.1)

1 INDICATIONS AND USAGE

KYXATA is a platinum-based drug indicated in adults:

- As part of a combination regimen, for the initial treatment of advanced ovarian carcinoma. (1.1)
- As a single-agent for the treatment of ovarian carcinoma recurrent after prior chemotherapy. (1.2)

2 DOSAGE AND ADMINISTRATION

- Initial Treatment of Advanced Ovarian Carcinoma:

- KYXATA 300 mg/m^2-OR-AUC of 4 mg/mL∙min to 6 mg/mL∙min intravenously in combination with cyclophosphamide on Day 1 every 4 weeks for each cycle. (2.2)
- Administer up to six cycles or until disease progression or unacceptable toxicity occurs. (2.2)

- Recurrent Advanced Ovarian Carcinoma as a Single Agent:

KYXATA 360 mg/m^2-OR- AUC of 4 mg/mL∙min to 6 mg/mL∙min intravenously on Day 1 every 4 weeks for each cycle until disease progression or unacceptable toxicity occurs. (2.2)

- Avoid contact of carboplatin with aluminum parts. (2.5)

3 DOSAGE FORMS AND STRENGTHS

- Injection: 20 mg/2 mL (10 mg/mL), 80 mg/8 mL (10 mg/mL), and 500 mg/50 mL (10 mg/mL) in multiple-dose vial. (3)

4 CONTRAINDICATIONS

- None. (4)

5 WARNINGS AND PRECAUTIONS

- Myelosuppression: Myelosuppression (leukopenia, neutropenia, and thrombocytopenia) can cause severe or fatal infections or hemorrhage. Monitor complete blood counts prior to each treatment cycle, and as clinically indicated. If myelosuppression occurs, modify KYXATA dosage. (5.2)
- Nausea and Vomiting: Administer pre-treatment and post-treatment antiemetics as clinically indicated. (5.3)
- Peripheral Neuropathy: Peripheral neuropathy, including paresthesia, can occur in patients treated with KYXATA. Monitor for signs and symptoms of peripheral neuropathy and modify the dosage of KYXATA based on severity. (5.4)
- Embryo-Fetal Toxicity: Can cause fetal harm. Advise patients of the potential risk to a fetus and to use effective contraception. (5.5, 8.1, 8.3)

6 ADVERSE REACTIONS

- Most common adverse reactions, including laboratory abnormalities, in patients with advanced ovarian cancer who received KYXATA in combination with cyclophosphamide (≥30%) are leukopenia, neutropenia, nausea and vomiting, anemia, thrombocytopenia, hypomagnesemia, other gastrointestinal adverse reactions, alopecia, asthenia, and pain. (6.1)
- Most common adverse reactions, including laboratory abnormalities, in patients with recurrent ovarian cancer who received KYXATA as a single agent (≥30%) are nausea and vomiting, anemia, neutropenia, thrombocytopenia, hyponatremia, hypomagnesemia, hyperphosphatasemia, and hypocalcemia. (6.1)

To report SUSPECTED ADVERSE REACTIONS, contact Avyxa Pharma, LLC at 1-888-520-0954 or FDA at 1-800-FDA-1088 or www.fda.gov/medwatch.

7 DRUG INTERACTIONS

- Aminoglycosides: Avoid concomitant use with aminoglycosides. (7.1)

8 USE IN SPECIFIC POPULATIONS

- Renal Impairment: Reduce the dose for patients with creatinine clearance of 16 to 59 mL/min who will be administered a dose based on body surface area. (8.6, 2.4)
- Lactation: Advise not to breastfeed. (8.2)

FULL PRESCRIBING INFORMATION

WARNING: HYPERSENSITIVITY REACTIONS, INCLUDING ANAPHYLAXIS

- Serious and life-threatening hypersensitivity reactions, including anaphylaxis, can occur with KYXATA within minutes of administration during any cycle.
- Immediately discontinue KYXATA for severe hypersensitivity reactions and administer appropriate treatment for management of the hypersensitivity reaction [see Warnings and Precautions (5.1)].

1 INDICATIONS AND USAGE

1.1 Initial Treatment of Advanced Ovarian Carcinoma

KYXATA, as part of a combination regimen, is indicated for the initial treatment of adults with advanced ovarian carcinoma.

1.2 Recurrent Advanced Ovarian Carcinoma

KYXATA is indicated for treatment of adults with ovarian carcinoma recurrent after prior chemotherapy.

2 DOSAGE AND ADMINISTRATION

2.1 Premedication and Supportive Medications

Administer KYXATA in a setting where cardiopulmonary resuscitation medication and equipment are available [see Warnings and Precautions (5.1)].

Premedicate patients with antiemetics prior to each infusion of KYXATA for the prevention of nausea and vomiting. Continue antiemetics following infusion as needed [see Warnings and Precautions (5.3)].

2.2 Recommended Dosage

Initial Treatment of Advanced Ovarian Carcinoma with Cyclophosphamide

- KYXATA 300 mg/m^2-OR-AUC of 4 mg/mL∙min to 6 mg/mL∙min* intravenously in combination with cyclophosphamide 600 mg/m^2intravenously on Day 1 every 4 weeks for each cycle.

*Carboplatin Dose (mg) = Target Area Under the Curve (AUC) (mg/mL/min) x (GFR + 25). Glomerular filtration rate (GFR) is commonly calculated as estimated creatinine clearance (CLcr) using the Cockroft-Gault formula.

- Administer up to six cycles or until disease progression or unacceptable toxicity occurs.

Refer to cyclophosphamide prescribing information for additional information.

For older adults, calculate the dose based on AUC to reduce risk of severe adverse reactions.

Individualize the dose and dosing schedule of KYXATA based on the specific regimen administered, response to treatment, and patient risk factors [see Dosage and Administration (2.3, 2.4)].

Secondary Treatment of Advanced Ovarian Carcinoma as a Single Agent

- KYXATA 360 mg/m^2-OR- AUC of 4 mg/mL∙min to 6 mg/mL∙min* intravenously on Day 1 every 4 weeks for each cycle until disease progression or unacceptable toxicity occurs.

* Carboplatin Dose (mg) = Target AUC (mg/mL/min) x (GFR + 25). GFR is commonly calculated as estimated creatinine clearance (CLcr) using the Cockroft-Gault formula.

For older adults, calculate the dose based on AUC to reduce risk of severe adverse reactions.

Individualize the dose and dosing schedule of KYXATA based on response to treatment and patient risk factors [see Dosage and Administration (2.3, 2.4)].

2.3 Dosage Modifications for Adverse Reactions

For a patients administered a dose based on body surface area as a single agent or combination, dosage modifications are shown in Table 1.

Monitor complete blood counts prior to treatment, weekly during treatment, and as clinically indicated [see Warnings and Precautions (5.2)].

Table 1: Recommended Dosage Modifications for Adverse Reactions for Patients Administered a Dose Based on Body-Surface Area
Adverse Reaction | Severity | Dosage Modification
Neutropenia [see Warnings and Precautions (5.2)] | Grade ≥ 4 ANC ≤ 0.5 x 10^9 / L | ● Interrupt KYXATA until ≤ Grade 1. ● Reduce dose by 25%
Thrombocytopenia [see Warnings and Precautions (5.2)] | Grade ≥ 3 Platelet count ≤ 50 x 10^9 / L | ● Interrupt KYXATA until ≤ Grade 1. ● Reduce dose by 25%

2.4 Dosage Recommendations for Patients with Renal Impairment

For patients administered a dose based on AUC, no dose modification is recommended for renal impairment.

For patients administered a dose based on body surface area, the recommended doses for renal impairment are described in Table 2 [see Use in Specific Populations (8.6) and Clinical Pharmacology (12.3)]. A recommended dose has not been established for patients with creatinine clearance <16 mL/min.

Table 2: Recommended Dose for Patients with Renal Impairment Administered a Dose Based on Body Surface Area
Creatinine Clearance (mL/min) | Recommended Dose on Day 1
60 to 89 | No dose reduction
41 to 59 | 250 mg/m^2
16 to 40 | 200 mg/m^2

2.5 Preparation and Administration

Preparation

KYXATA is a hazardous drug. Follow applicable handling and disposal procedures.^1

Do not use needles or intravenous infusion sets containing aluminum; aluminum reacts with carboplatin causing precipitate formation and a loss of potency.

Visually inspect KYXATA vials prior to use. Discard solution if particulate matter or discoloration are observed.

KYXATA is supplied as a multiple-dose vial. After first use, store the partially used vial in the original carton at 20°C to 25°C (68°F to 77°F) and then discard after 28 days.

- Withdraw the calculated dose of KYXATA from the vial.
- Prior to administration, KYXATA can be further diluted to concentrations as low as 0.5 mg/mL with 5% Dextrose Injection, USP or 0.9% Sodium Chloride Injection, USP.
- Diluted carboplatin solution for infusion when prepared as directed in an infusion bag should be used immediately, but may be stored at room temperature (20°C to 25°C) for a maximum of 8 hours. Discard KYXATA infusion solution 8 hours after dilution.

Administration

Administer KYXATA by intravenous infusion over 30 to 60 minutes.

3 DOSAGE FORMS AND STRENGTHS

Injection: 20 mg/2 mL (10 mg/mL), 80 mg/8 mL (10 mg/mL), and 500 mg/50 mL (10 mg/mL) available as clear to pale yellow solution in multiple-dose vials.

4 CONTRAINDICATIONS

None.

5 WARNINGS AND PRECAUTIONS

5.1 Hypersensitivity Reactions

Hypersensitivity, including anaphylaxis, can occur in patients treated with KYXATA. Hypersensitivity reactions occurred in 2% of patients treated with carboplatin and included rash, urticaria, erythema, pruritus, bronchospasm, and hypotension. These adverse reactions may occur within minutes of administration and during any cycle. There is an increased risk of allergic reactions, including anaphylaxis, in patients previously exposed to platinum-based therapy or after 6 cycles of carboplatin [see Adverse Reactions (6.1)].

Monitor patients receiving KYXATA for hypersensitivity reactions. Ensure supportive equipment and medications are available to treat severe hypersensitivity reactions. Severe hypersensitivity reactions may require immediate discontinuation of KYXATA.

5.2 Myelosuppression

Myelosuppression (leukopenia, neutropenia, and thrombocytopenia) is dose-dependent may be severe, and can cause fatal infections or hemorrhage in patients treated with KYXATA.

Grade 3–4 neutropenia occurred in 16% of the patients treated with carboplatin as a single agent. Grade 3-4 thrombocytopenia occurred in 25% of patients with ovarian cancer. Febrile neutropenia may occur. Blood product transfusions were required in 26% (44% of pretreated) of patients with ovarian cancer treated with carboplatin as a single agent. Infectious and hemorrhagic complications each occurred in 5% of the patients treated with carboplatin as a single agent. Fatal adverse reactions occurred in less than 1% of patients treated with carboplatin as a single agent.

Patients with impaired kidney function are at increased risk of severe myelosuppression and may require dosage modifications [see Dosage and Administration (2.4) and Use in Specific Populations (8.6)].

Monitor complete blood counts prior to each cycle and as clinically indicated. If myelosuppression occurs, modify KYXATA dosage when required [see Dosage and Administration (2.3)].

5.3 Nausea and Vomiting

KYXATA can induce emesis, which can be more severe in patients previously receiving emetogenic therapy, and is dose-dependent. Administer pre-treatment and post-treatment antiemetics as clinically indicated [see Dosage and Administration (2.1)].

Monitor and manage patients with antiemetics, or fluid replacement, as clinically indicated. Consider withholding or delaying KYXATA if nausea or vomiting is severe or intolerable and is not responsive to antiemetics.

5.4 Peripheral Neuropathy

Peripheral neuropathy, including paresthesia, can occur in patients treated with KYXATA.

Peripheral neuropathy occurred in 4% of patients receiving carboplatin as a single agent (6% of pretreated patients with ovarian cancer). Peripheral neuropathy occurred in 10% of patients older than 65 who were previously treated with carboplatin.

Prolonged treatment, treatment with other platinum-containing therapies, or use in combination with other drugs that cause peripheral neuropathy may increase the incidence or severity of peripheral neuropathy.

Monitor for signs and symptoms of peripheral neuropathy. Withhold, reduce, or discontinue KYXATA depending on the severity and persistence of peripheral neuropathy as clinically indicated.

5.5 Embryo-Fetal Toxicity

Based on findings in animals and its mechanism of action, KYXATA can cause fetal harm when administered to a pregnant woman [see Clinical Pharmacology (12.1)]. Administration of carboplatin to pregnant rats caused adverse developmental outcomes, including embryo-fetal lethality and structural abnormalities.

Advise pregnant women and females of reproductive potential of the potential risk to a fetus. Advise females of reproductive potential to use effective contraception during treatment with KYXATA and for 6 months after the last dose. Advise males with female partners of reproductive potential to use effective contraception during treatment with KYXATA and for 3 months after the last dose [see Use in Specific Populations (8.1,8.3)].

6 ADVERSE REACTIONS

The following clinically significant adverse reactions are described elsewhere in the labeling:

- Hypersensitivity [see Warnings and Precautions (5.1)]
- Myelosuppression [see Warnings and Precautions (5.2)]
- Nausea and Vomiting [see Warnings and Precautions (5.3)]
- Peripheral Neuropathy [see Warnings and Precautions (5.4)]

6.1 Clinical Trials Experience

Because clinical trials are conducted under widely varying conditions, adverse reaction rates observed in the clinical trials of a drug cannot be directly compared to rates in the clinical trials of another drug and may not reflect the rates observed in clinical practice.

Initial Treatment of Advanced Ovarian Cancer

The safety of KYXATA in combination with cyclophosphamide for initial treatment of advanced ovarian cancer was evaluated in two randomized controlled studies conducted by NCIC and SWOG [see Clinical Studies (14.1)]. Patients in the carboplatin arm received carboplatin in combination with cyclophosphamide and patients in the active-comparator arm received cisplatin in combination with cyclophosphamide.

Tables 3 and 4 summarize the adverse reactions and laboratory abnormalities in the NCIC study, respectively.

Table 3: Adverse Reactions (≥ 5%) in Patients with Advanced Ovarian Cancer - NCIC Study
Adverse Reaction | Carboplatin in combination with cyclophosphamide (N=224) (%)* | Cisplatin in combination with cyclophosphamide (N=223) (%)*
Gastrointestinal (GI)
Nausea and vomiting | 93 | 98
Vomiting | 84 | 97
Other GI adverse reactions | 50 | 62
Mucositis | 10 | 9
Skin and Subcutaneous Tissue
Alopecia | 50 | 62
General
Asthenia | 40 | 33
Pain | 36 | 37
Cardiovascular | 15 | 19
Infection | 14 | 12
Hypersensitivity | 12 | 9
Hemorrhage | 10 | 4
Genitourinary | 10 | 10
Respiratory | 8 | 9
Neurologic
Central neurotoxicity | 28 | 40
Peripheral neuropathies | 16 | 42
Ototoxicity | 13 | 33
Other sensory disorders | 6 | 10
* Values are in percent of evaluable patients.

Table 4: Laboratory Abnormalities in Patients with Advanced Ovarian Cancer - NCIC Study
Laboratory Abnormality | Carboplatin in combination with cyclophosphamide (N=224)* | Cisplatin in combination with cyclophosphamide (N=223)*
Laboratory Abnormality | (%) | (%)
Hematology
Decreased neutrophils <2000 cells/mm^3 | 97 | 96
Decreased neutrophils <1000 cells/mm^3 | 81 | 79
Decreased hemoglobin <11 g/dL | 91 | 91
Decreased hemoglobin <8 g/dL | 18 | 12
Decreased platelets <100,000/mm^3 | 70 | 29
Decreased platelets <50,000/mm^3 | 41 | 6
Chemistry
Decreased magnesium | 63 | 88
Increased blood urea nitrogen | 17 | 31
Increased AST | 17 | 13
Decreased potassium | 16 | 22
Decreased calcium | 16 | 19
Decreased sodium | 10 | 20
Increased serum creatinine | 5 | 13
Increased bilirubin | 5 | 3
* Values are in percent of evaluable patients.

Tables 5 and 6 summarize the adverse reactions and laboratory abnormalities in the SWOG study, respectively.

Table 5: Adverse Reactions (≥ 5%) in Patients with Ovarian Cancer – SWOG Study
Adverse Reaction | Carboplatin in combination with cyclophosphamide (N=171) (%)* | Cisplatin in combination with cyclophosphamide (N=171) (%)*
Gastrointestinal (GI)
Nausea and vomiting | 94 | 96
Vomiting | 82 | 91
Other GI side effects | 40 | 48
General
Pain | 54 | 52
Alopecia | 43 | 57
Asthenia | 43 | 46
Cardiovascular | 23 | 30
Respiratory | 12 | 11
Genitourinary | 11 | 13
Hypersensitivity | 10 | 11
Mucositis | 6 | 11
Neurologic
Central neurotoxicity | 23 | 29
Peripheral neuropathies | 13 | 28
Ototoxicity | 12 | 30
Other sensory side effects | - | 6
* Values are in percent of evaluable patients.

Table 6: Laboratory Abnormalities in Patients with Advanced Ovarian Cancer - SWOG Study
Laboratory Abnormality | Carboplatin in combination with cyclophosphamide (N=171) (%)* | Cisplatin in combination with cyclophosphamide (N=171) (%)*
Hematology
Decreased neutrophils <2000 cells/mm^3 | 95 | 97
Decreased neutrophils <1000 cells/mm^3 | 84 | 78
Decreased hemoglobin <11 g/dL | 88 | 87
Decreased hemoglobin <8 g/dL | 8 | 24
Decreased platelets <100,000/mm^3 | 59 | 35
Decreased platelets <50,000/mm^3 | 22 | 11
Chemistry
Decreased magnesium | 58 | 77
Increased alkaline phosphatase | 29 | 20
Increased AST | 23 | 16
Increased serum creatinine | 7 | 38
Increased bilirubin | 5 | -
* Values are in percent of evaluable patients.

Recurrent Ovarian Cancer

The safety of carboplatin as a single agent for patients with ovarian carcinoma recurrent after prior chemotherapy was evaluated in two prospective, randomized controlled studies [see Clinical Studies (14.2)].

Tables 7 and 8 summarize the adverse reactions and laboratory abnormalities from these studies, respectively

Table 7: Adverse Reactions (≥5%) in Patients Treated with Carboplatin (Single-agent) for Advanced Ovarian Cancer in Two Controlled Studies
Adverse Reaction | Carboplatin as a Second Line Single-Agent Therapy N=553 (%)
Gastrointestinal (GI)
Nausea and vomiting | 92
Vomiting | 81
Other GI side effects | 21
Neurologic
Pain | 23
Asthenia | 11
Peripheral neuropathies | 6
Central neurotoxicity | 5
General
Cardiovascular | 6
Respiratory | 6
Infections | 5
Bleeding | 5

Clinically relevant adverse reactions in < 5% of patients who received carboplatin included allergic reactions, alopecia, mucositis, ototoxicity, and sensory disorders.

Table 8: Laboratory Abnormalities in Patients Treated with Carboplatin as a Single-agent for Secondary Treatment of Advanced Ovarian Cancer in Two Prospective, Randomized Controlled Studies
Laboratory Abnormality | Carboplatin as a Second Line Single-Agent Therapy N=553 (%)
Hematology
Decreased hemoglobin <11 g/dL | 90
Decreased hemoglobin <8 g/dL | 21
Decreased neutrophils <2000 cells/mm^3 | 67
Decreased neutrophils <1000 cells/mm^3 | 21
Decreased platelets <100,000/mm^3 | 62
Decreased platelets <50,000/mm^3 | 35
Chemistry
Decreased sodium | 47
Decreased magnesium | 43
Increased alkaline phosphatase | 37
Decreased calcium | 31
Decreased potassium | 28
Increased blood urea | 22
Increased AST | 19
Increased serum creatinine | 10
Increased bilirubin | 5

Other Clinical Trials Experience

The following adverse reactions occurred in patients treated with carboplatin for ovarian cancer as a single agent or in combination with chemotherapy in clinical trials:

The following adverse reactions occurred in patients (n=1893) with solid tumors or hematological malignancies treated with single agent carboplatin in clinical trials:

Gastrointestinal Disorders: diarrhea (6%), constipation (6%), dysgeusia (1%)

Ocular Disorders: visual disturbances (1%).

The following adverse reactions occurred in patients treated with carboplatin for ovarian cancer in combination with chemotherapy in clinical trials:

Cardiovascular: arterial thromboembolic event, venous thromboembolic event

General: fatigue, febrile neutropenia

Musculoskeletal and Connective Tissue Disorders: fistula, wound-healing complication

Renal and Urinary Disorders: proteinuria

Respiratory: dyspnea

6.2 Postmarketing Experience

The following adverse reactions have been identified during post approval use of carboplatin. Because these reactions are reported voluntarily from a population of uncertain size, it is not always possible to reliably estimate their frequency or establish a causal relationship to drug exposure.

- Allergic reactions: anaphylaxis, bronchospasm, erythema, hypotension, pruritus, rash, urticaria
- Blood and Lymphatic System:hemolytic uremic syndrome, secondary acute myeloid leukemia
- Cardiovascular: cardiac failure, cerebrovascular accident, embolism, hemorrhage, hypertension
- Gastrointestinal:stomatitis
- General disorders:anorexia, dehydration, injection site reactions (including redness, pain, swelling, extravasation, and necrosis), malaise
- Infection:sepsis/septic shock
- Renal and Urinary Disorders: acute kidney injury

7 DRUG INTERACTIONS

7.1 Use with Aminoglycosides

Avoid concomitant use of aminoglycosides with KYXATA. Concomitant use of KYXATA with aminoglycosides increased renal toxicity and ototoxicity.

8 USE IN SPECIFIC POPULATIONS

8.1 Pregnancy

Risk Summary

Based on findings from animals and its mechanism of action [see Clinical Pharmacology (12.1)], KYXATA can cause fetal harm when administered to a pregnant woman. Available data from case reports with carboplatin use in pregnant women are insufficient to inform a drug-associated risk. Administration of carboplatin to pregnant rats caused adverse developmental outcomes, including embryo-lethality and structural abnormalities (see Data). Advise pregnant women and females of reproductive potential of the potential risk to a fetus.

In the U.S. general population, the estimated background risk of major birth defects and miscarriage in clinically recognized pregnancies is 2% to 4% and 15% to 20%, respectively.

Data

Animal Data

Carboplatin administered to pregnant rats was embryo-lethal and teratogenic.

8.2 Lactation

Risk Summary

There are limited data on the presence of carboplatin or its metabolites in human milk, its effects on a breastfed child, or its effects on milk production. Because of the potential for serious adverse reactions in a breastfed child, advise women not to breastfeed during treatment with KYXATA and for 1 week after the last dose.

8.3 Females and Males of Reproductive Potential

KYXATA can cause fetal harm when administered to a pregnant woman [see Use in Specific Populations (8.1)].

Pregnancy Testing

Verify pregnancy status in females of reproductive potential prior to initiating KYXATA.

Contraception

Females

Advise females of reproductive potential to use effective contraception during treatment with KYXATA and for 6 months after the last dose.

Males

Based on genotoxicity findings, advise male patients with female partners of reproductive potential to use effective contraception during treatment with KYXATA and for 3 months after the last dose [see Nonclinical Toxicology (13.1)].

8.4 Pediatric Use

The safety and effectiveness of KYXATA in pediatric patients have not been established.

Pediatric patients may be at risk of hearing loss if KYXATA is administered at higher than recommended dosages or in combination with other ototoxic agents.

8.5 Geriatric Use

Of the 395 patients treated with carboplatin in combination with cyclophosphamide, 141 (36%) were over 65 years of age, and 22 (6%) were 75 years and older [see Clinical Studies (14.1)].

No overall differences in effectiveness were observed between these patients and younger patients.

Elderly patients treated with carboplatin were more likely to develop severe thrombocytopenia or peripheral neuropathy than younger patients [see Warnings and Precautions (5.2, 5.4)]

Of the 1,942 patients with solid tumors or hematological malignancies from pooled clinical trials that received single-agent carboplatin, 414 (21%) were 65 years of age and older, and a similar incidence of other adverse reactions was seen in these older patients compared to patients less than 65 years of age.

Consider renal function when selecting the KYXATA dose for older adults since they often have decreased renal function. To minimize the risk of toxicity in older adults, calculate the dose based on AUC [see Dosage and Administration (2.3)].

8.6 Renal Impairment

For patients administered a dose based on AUC, no dose modification is recommended for renal impairment.

For patients administered a dose based on body surface area, reduce the dose if creatinine clearance (CLcr) is 16 to 59 mL/min [see Dosage and Administration (2.4)]. A recommended dose of KYXATA has not been established for patients with CLcr <16 mL/min.

Patients with impaired renal function are at increased risk of myelosuppression [see Warnings and Precautions (5.2)].

10 OVERDOSAGE

There is no known antidote for KYXATA overdosage. The anticipated complications of overdosage would be secondary to bone marrow suppression and/or hepatic toxicity. Patients receiving overdosages of carboplatin experienced severe liver function test abnormalities. Loss of vision, which can be complete for light and colors, has been reported after the use of carboplatin at doses higher than the recommended approved dosage for KYXATA. Vision recovers totally or to a significant extent after discontinuation of carboplatin. Clinically significant hearing loss has been reported to occur in pediatric patients when carboplatin was administered at higher than approved recommended doses for KYXATA and in combination with other ototoxic agents [see Drug Interactions (7)]. KYXATA is removed by dialysis.

Closely monitor patients suspected of receiving an overdose, including for the adverse reactions described above, and administer appropriate supportive treatment.

11 DESCRIPTION

KYXATA is a platinum-based drug. The chemical name for carboplatin is platinum, diammine [1,1- cyclobutane-dicarboxylato(2-)-0,0']-,(SP-4-2) and carboplatin has the following structural formula:

Carboplatin is a white crystalline powder with the molecular formula of C6H12N2O4Pt and a molecular weight of 371.26 g/mol. It is sparingly soluble in water and very slightly soluble in acetone and in alcohol. The pH of a 1% carboplatin solution in water is 5 to 7.

KYXATA (carboplatin) injection is supplied as a sterile, clear to pale yellow solution as 20 mg/2 mL, 80 mg/8mL, 500 mg/50 mL in multiple-dose vials for administration by intravenous infusion. Each mL contains 10 mg carboplatin.

12 CLINICAL PHARMACOLOGY

12.1 Mechanism of Action

Carboplatin is a platinum-based drug that binds to DNA and forms DNA cross-links. These crosslinks inhibit DNA replication and transcription and trigger cytotoxic processes that lead to cell death.

12.2 Pharmacodynamics

Carboplatin exposure-response relationships and the time course of pharmacodynamic response have not been fully characterized.

12.3 Pharmacokinetics

Carboplatin pharmacokinetics were observed in patients with creatinine clearance (CLcr) of about 60 mL/min or greater following a dose of 300 mg/m^2 to 500 mg/m^2as an intravenous infusion over 30-minutes. The Cmax and AUC0-INF increase linearly with dose, although the increase was slightly more than dose proportional.

Distribution

The volume of distribution is 16 L.

Carboplatin is not bound to plasma proteins. No significant quantities of protein-free, ultrafilterable platinum-containing species other than carboplatin are present in plasma. However, platinum from carboplatin becomes irreversibly bound to plasma proteins.

Elimination

The elimination half-life is 2.6 to 5.9 hours and the total body clearance is 4.4 L/hour.

The elimination half-life of platinum from carboplatin bound to plasma proteins is a minimum of 5 days.

Excretion

The major route of elimination of carboplatin is renal excretion with 65% of the dose excreted in the urine within 12 hours and 71% within 24 hours. All of the platinum in the 24-hour urine is present as carboplatin.

Specific Populations

Renal Impairment: In patients with CLcr below 60 mL/min, the total body and renal clearances of carboplatin decrease as renal function decreases.

13 NONCLINICAL TOXICOLOGY

13.1 Carcinogenesis, Mutagenesis, Impairment of Fertility

The carcinogenic potential of carboplatin has not been studied, but compounds with similar mechanisms of action and mutagenicity profiles are carcinogenic.

Carboplatin is mutagenic both in vitro and in vivo.

14 CLINICAL STUDIES

14.1 Use with Cyclophosphamide for Initial Treatment of Ovarian Cancer

The efficacy of carboplatin was evaluated in additional two randomized, controlled studies conducted by the National Cancer Institute of Canada, Clinical Trials Group (NCIC) and the Southwest Oncology Group (SWOG) in patients with advanced ovarian cancer.

Table 9: Overview of the NCIC and SWOG Trials
Overview of Pivotal Trials
 | NCIC | SWOG
Number of patients | 447 | 342
Median age (years) | 60 | 62
Dose of cisplatin | 75 mg/m^2 | 100 mg/m^2
Dose of carboplatin | 300 mg/m^2 | 300 mg/m^2
Dose of cyclophosphamide | 600 mg/m^2 | 600 mg/m^2
Residual tumor <2 cm (number of patients) | 39% (174/447) | 14% (49/342)

The efficacy results from the NCIC Trial are shown below in Table 10.

Table10: Efficacy Results for the NCIC Trial
 | Carboplatin in combination with cyclophosphamide | Cisplatin in combination with cyclophosphamide
Overall Survival
Median OS in months | 25.3 | 22.8
Hazard ratio (95% CI) | 0.98 (0.78, 1.23)
2-year Survivala | 51.9% | 40.2%
3-year Survivala | 34.6% | 33.1%
Progression-free Survival
Median PFS in months | 13.6 | 14
Hazard ratio (95% CI) | 1.10 (0.89, 1.35)
2-year PFSa | 31% | 31%
3-year PFSa | 19% | 23%
Response Rates
Pathologic Complete Response, n (%)b | 24/224 (11%) | 33/223 (15%)
Clinical Response in Measurable Patients (%) | 60% | 58%
a Kaplan-Meier Estimates
b 114 carboplatin and 109 cisplatin patients did not undergo second look surgery in NCIC study.

The efficacy results from the SWOG trial are shown below in Table 11.

Table 11: Efficacy Results for the SWOG Trial
 | Carboplatin in combination with cyclophosphamide | Cisplatin in combination with cyclophosphamide
Overall Survival
Median OS in months | 19.8 | 18.2
Hazard ratio (95% CI) | 1.01 (0.78, 1.30)
2-year Survivala | 40.2% | 39.0%
3-year Survivala | 18.3% | 24.9%
Progression-free Survival
Median PFS in months | 11.3 | 10.8
Hazard ratio (95% CI) | 1.02 (0.81, 1.29)
2-year PFSa | 21% | 21%
3-year PFSa | 8% | 14%
Response Rates
Pathologic Complete Response, n (%)b | 17/171 (10%) | 17/171 (10%)
Clinical Response in Measurable Patients (%) | 58% | 43%
a Kaplan-Meier Estimates
b 90 carboplatin and 106 cisplatin patients did not undergo second look surgery in SWOG study.

14.2 Use as a Single Agent for Secondary Treatment of Advanced Ovarian Cancer

In two prospective, randomized controlled studies in 47 patients with advanced ovarian cancer previously treated with chemotherapy who were treated with carboplatin as a single agent, 13% (6/47) of patients had clinical complete responses. The duration of these responses ranged from 45 to 71+ weeks. Within the group of patients previously treated with cisplatin, those who have developed progressive disease while receiving cisplatin therapy may have a decreased response rate.

15 REFERENCES

1. "OSHA Hazardous Drugs." OSHA. http://www.osha.gov/SLTC/hazardousdrugs/index.html

16 HOW SUPPLIED/STORAGE AND HANDLING

How Supplied

KYXATATM (carboplatin) injection is supplied as clear to pale yellow solution in the following presentations:

Unit of Sale | Strength
NDC 83831-140-02 Carton containing 1 multiple-dose vial (Light Blue flip-off seals) | 20 mg/2 mL (10 mg/mL)
NDC 83831-141-08 Carton containing 1 multiple-dose vial (Green flip-off seals) | 80 mg/8 mL (10 mg/mL)
NDC 83831-142-50 Carton containing 1 multiple-dose vial (Grey flip-off seals) | 500 mg/50 mL (10 mg/mL)

Storage and Handling

Store at 20°C to 25°C (68°F to 77°F); excursions permitted from 15°C to 30°C (59°F to 86°F) [see USP Controlled Room Temperature]. Protect from light.

KYXATA is a hazardous drug. Follow applicable special handling and disposal procedures.^1

17 PATIENT COUNSELING INFORMATION

Advise the patient to read the FDA-approved patient labeling (Patient Information).

Hypersensitivity

Inform patients that KYXATA can cause hypersensitivity reactions, including anaphylaxis. and to immediately report signs or symptoms of hypersensitivity reactions to their healthcare provider. Advise patients to seek medical attention immediately if they experience severe symptoms [see Warnings and Precautions (5.1)].

Myelosuppression

Inform patients that KYXATA can cause myelosuppression to immediately report signs or symptoms such as bleeding, easy bruising, symptoms of infection (fever, chills, cough, pain, or burning during urination), fatigue, or shortness of breath to their healthcare provider. Advise patients that complete blood counts will be monitored at baseline, during treatment, and as clinically indicated [see Warnings and Precautions (5.2)].

Nausea and Vomiting

Advise patients about the use of antiemetics to prevent nausea and vomiting and to report persistent or severe symptoms to their healthcare provider [see Warnings and Precautions (5.3)].

Peripheral Neuropathy

Advise patients to report any new paresthesia to their healthcare provider [see Warnings and Precautions (5.4)].

Embryo-Fetal Toxicity

Advise pregnant women and females of reproductive potential of the potential risk to a fetus and to inform their healthcare provider of a known or suspected pregnancy [see Warnings and Precautions (5.5), Use in Specific Populations (8.1)].

Advise females of reproductive potential to use effective contraception during treatment with KYXATA and for 6 months after the last dose [see Use in Specific Populations (8.3)].

Advise male patients with female partners of reproductive potential to use effective contraception during treatment with KYXATA and for 3 months after the last dose [see Use in Specific Populations (8.3)].

Lactation

Advise women not to breastfeed during treatment with KYXATA and for 1 week after the last dose [see Use in Specific Populations (8.2)].

Manufactured for:

Avyxa Pharma, LLC

New Jersey 07054, USA

Made in Switzerland

SPL PATIENT PACKAGE INSERT

Patient Information
KYXATATM (Kix-ZAT-ah)
(carboplatin) injection
for intravenous use

What is the most important information I should know about KYXATA?
KYXATA can cause allergic reactions, including serious allergic reactions that can be life-threatening. KYXATA is a platinum-based medicine. Serious allergic reactions can happen in people who take KYXATA and who have had a previous allergic reaction to platinum-based medicines. Serious allergic reactions can happen within a few minutes of your KYXATA infusion or any time during your treatment with KYXATA.
Tell your healthcare provider or get emergency medical help right away if you:
● have trouble breathing
● feel like your throat is closing up
Call your healthcare provider right away if you get any of the following signs or symptoms of an allergic reaction:

● rash
● flushed face
● hives
● itching
● swelling of your lips or tongue

● sudden cough
● dizziness or feel faint
● sweating
● chest pain

See "What are the possible side effects of KYXATA?" for more information about side effects.

What is KYXATA?
KYXATA is a prescription medicine used to treat adults:
● in combination with another chemotherapy medicine, for your first treatment of advanced ovarian cancer.
● alone when your ovarian cancer has come back (recurrent) after you have been treated with prior chemotherapy medicines.
It is not known if KYXATA is safe and effective in children.

Before you receive KYXATA tell your healthcare provider about all of your medical conditions, including if you:
● have kidney problems
● are pregnant or plan to become pregnant. KYXATA can harm your unborn baby.
Females who are able to become pregnant:
○ Your healthcare provider will check to see if you are pregnant before you start treatment with KYXATA.
○ Use effective birth control (contraception) during treatment with KYXATA and for 6 months after your last dose.
○ Tell your healthcare provider right away if you become pregnant or think you may be pregnant during treatment with KYXATA.
Males with female partners who are able to become pregnant:
○ Use effective birth control (contraception) during treatment with KYXATA and for 3 months after your last dose.
○ Tell your healthcare provider right away if your female partner becomes pregnant or thinks she may be pregnant during your treatment with KYXATA.
● are breastfeeding or plan to breastfeed. It is not known if KYXATA passes into your breast milk. Do not breastfeed during treatment with KYXATA and for 1 week after your last dose of KYXATA. Talk to your healthcare provider about the best way to feed your baby during this time.
Tell your healthcare provider about all the medicines you take , including prescription and over‑the‑counter medicines, vitamins, and herbal supplements.

How will I receive KYXATA?
● Your healthcare provider will give you KYXATA into your vein as an intravenous (IV) infusion over 30 to 60 minutes.
● Your healthcare provider will give you medicines before each KYXATA infusion to help prevent nausea and vomiting and may continue these medicines after your infusion as needed.
● For advanced ovarian cancer, KYXATA may be given in combination with another chemotherapy medicine on Day 1 of each cycle. Your healthcare provider will decide how often KYXATA is given based on the other chemotherapy medicine used with KYXATA.
● For recurrent ovarian cancer, KYXATA may be given alone on Day 1 every 4 weeks (1 cycle).
● Your healthcare provider will decide how many treatments you need.
● Your healthcare provider may change your dose of KYXATA, or tell you to stop KYXATA for a short period of time or permanently if you have certain side effects.

What are the possible side effects of KYXATA?
KYXATA can cause serious side effects, including:
See "What is the most important information about KYXATA?" above.
● Low blood cell counts . Decreased red blood cells, white blood cells, and platelets are common with KYXATA, but can also be severe and lead to bleeding or infections that can cause death. Some people have needed blood transfusions. Your healthcare provider will do blood tests before you start and during treatment with KYXATA to check your blood cell counts. Tell your healthcare provider right away if you develop a fever of 100.5°F or greater or get any of the following signs or symptoms:

○ chills or shivering
○ cough
○ pain
○ burning or pain on urination

○ feeling tired
○ shortness of breath
○ unusual bruising or bleeding
○ black tarry stools
○ blood in your urine

● Nausea and vomiting. Nausea and vomiting are common during treatment with KYXATA but can also be severe. Before each infusion of KYXATA, you will receive medicines to help prevent nausea and vomiting. You may receive medicines after your infusion if needed. Tell your healthcare provider right away if you have severe nausea or vomiting that does not stop.
● Peripheral neuropathy. Tell your healthcare provider if you develop tingling, numbness, or burning (feel like "pins and needles") in your hands or feet.
The most common side effects in adults with advanced ovarian cancer who received KYXATA in combination with another chemotherapy medicine include:

● decreased white blood cells
● nausea and vomiting
● decreased red blood cells (anemia)
● decreased platelets
● decreased magnesium

● diarrhea
● constipation
● hair loss
● weakness
● pain

The most common side effects in adults with recurrent ovarian cancer who received KYXATA alone include:

● nausea and vomiting
● decreased red blood cells (anemia)
● decreased white blood cells
● decreased platelets

● decreased sodium
● decreased magnesium
● increased alkaline phosphatase
● decreased calcium

These are not all the possible side effects of KYXATA.
Call your doctor for medical advice about side effects. You may report side effects to FDA at 1-800-FDA-1088.

General information about the safe and effective use of KYXATA.
Medicines are sometimes prescribed for purposes other than those listed in a Patient Information leaflet. You can ask your healthcare provider or pharmacist for more information about KYXATA that is written for health professionals.

What are the ingredients in KYXATA?
Active ingredient: carboplatin

Manufactured for:
Avyxa Pharma, LLC
New Jersey 07054, USA
Made in Switzerland
For more information, call 1-888-520-0954.

This Patient Information has been approved by the U.S. Food and Drug Administration. Issued: 09/2025

PACKAGE LABEL.PRINCIPAL DISPLAY PANEL

KYXATA (CARBOplatin) Injection, 80 mg/8 mL (10 mg/mL) -Vial Label
KYXATA (CARBOplatin) Injection, 80 mg/8 mL (10 mg/mL) -Carton Label
KYXATA (CARBOplatin) Injection, 500 mg/50 mL (10 mg/mL) -Vial Label
KYXATA (CARBOplatin) Injection, 500 mg/50 mL (10 mg/mL) -Carton Label